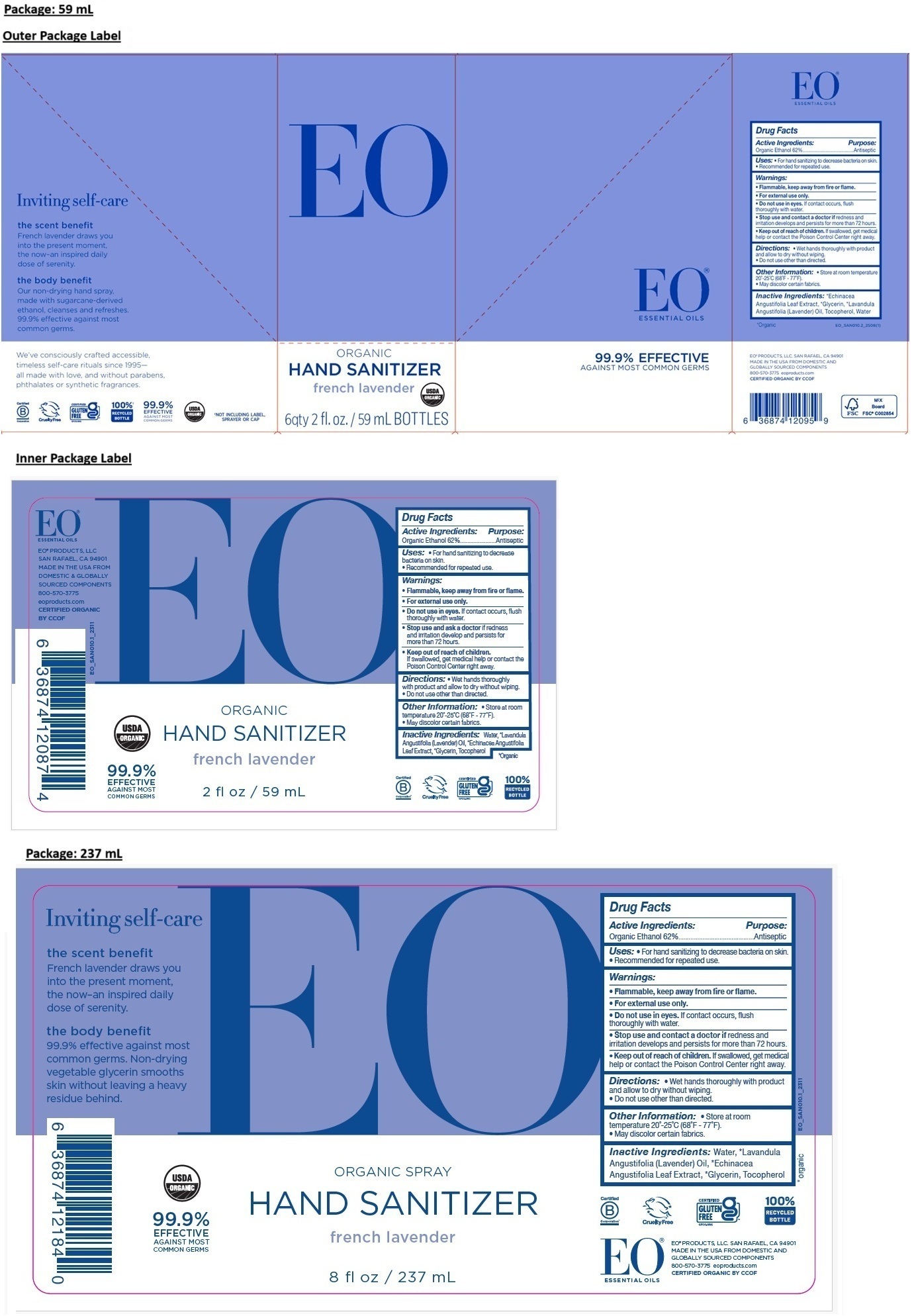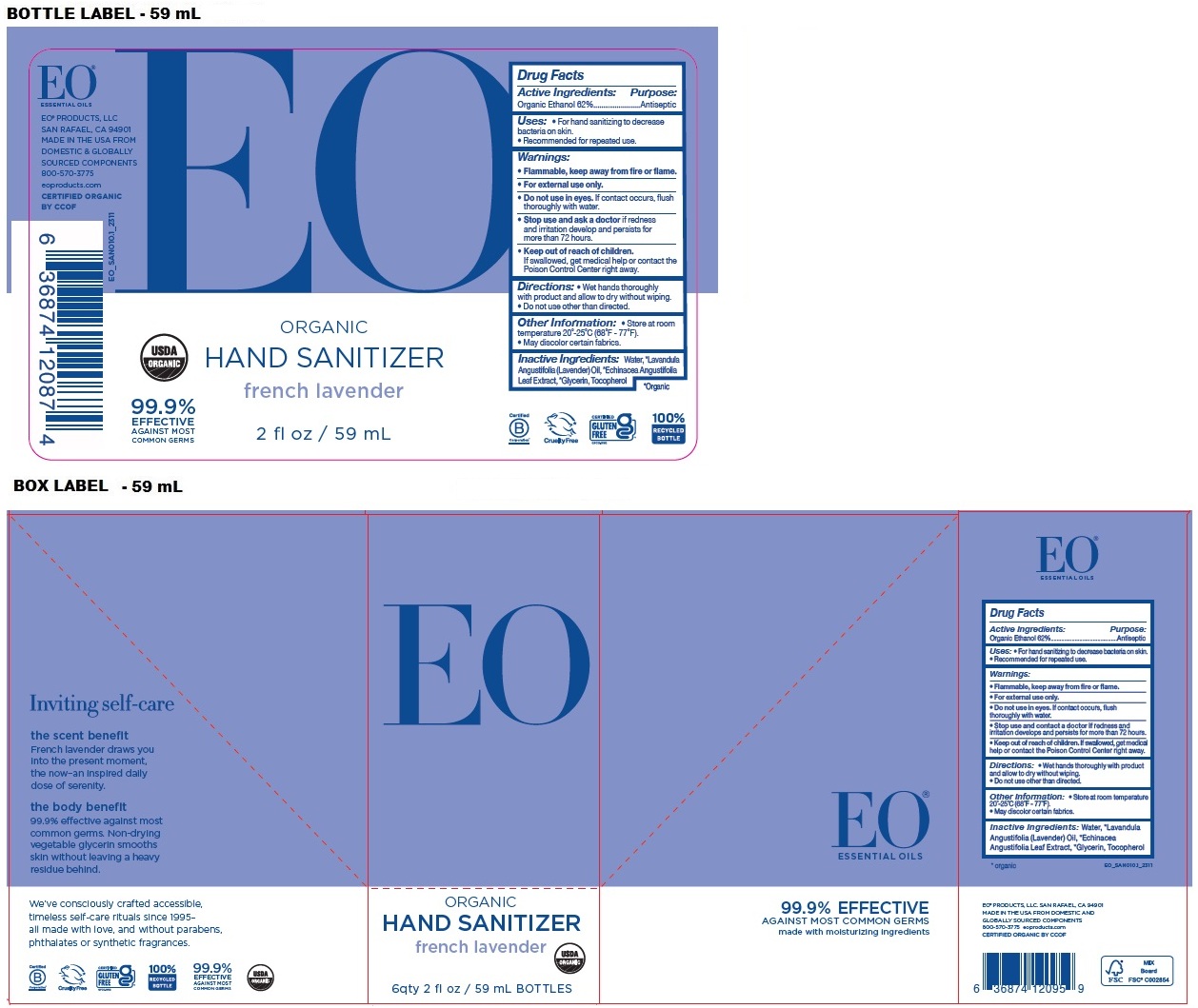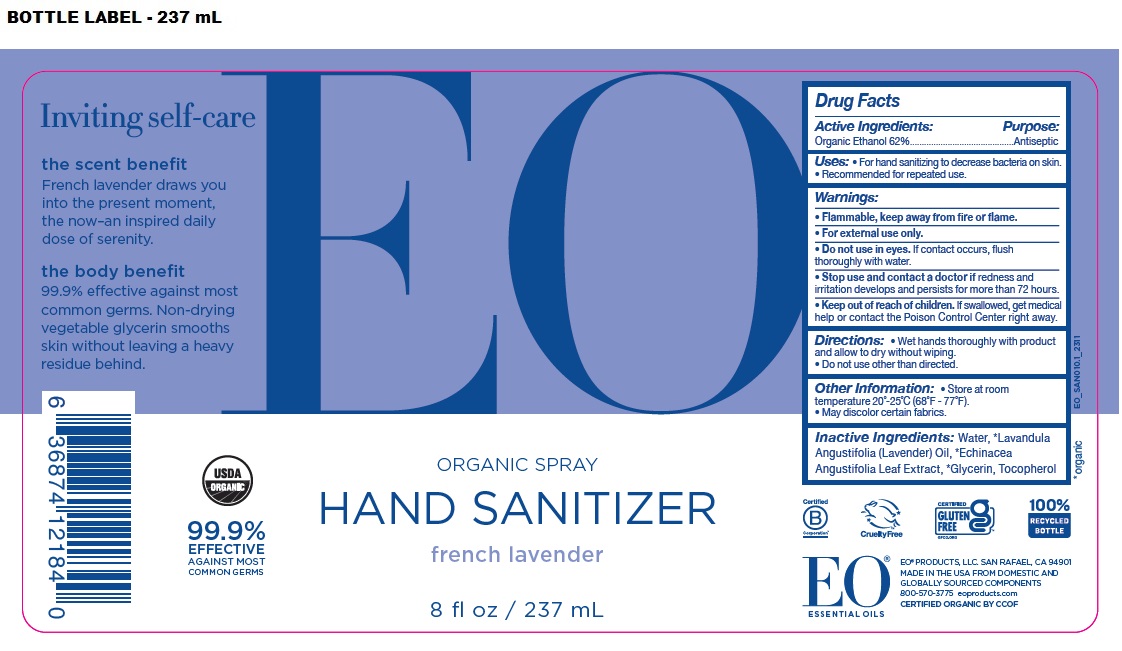 DRUG LABEL: EO HAND SANITIZER
NDC: 54748-101 | Form: SPRAY
Manufacturer: EO Products, LLC
Category: otc | Type: HUMAN OTC DRUG LABEL
Date: 20251121

ACTIVE INGREDIENTS: ALCOHOL 62 mL/100 mL
INACTIVE INGREDIENTS: ECHINACEA ANGUSTIFOLIA LEAF; GLYCERIN; LAVENDER OIL; TOCOPHEROL; WATER

EO ORGANIC HAND SANITIZER french lavender

Active Ingredients:

Organic Ethanol 62%

Purpose:

Antiseptic

Uses:

• For hand sanitizing to decrease bacteria on skin.
• Recommended for repeated use.

Warnings:

• Flammable, keep away from fire or flame.

• For external use only.

• Do not use in eyes. If contact occurs, flush thoroughly with water.

• Stop use and contact a doctor if redness and irritation develops and persists for more than 72 hours.

• Keep out of reach of children. If swallowed, get medical help or contact the Poison Control Center right away.

Directions:

• Wet hands thoroughly with product and allow to dry without wiping.
• Do not use other than directed.

Other Information:

• Store at room temperature 20°-25°C (68°F - 77°F).
• May discolor certain fabrics.

Inactive Ingredients:

*Echinacea Angustifolia Leaf Extract, *Glycerin, *Lavandula Angustifolia (Lavender) Oil, Tocopherol, Water

*Organic

USDA ORGANIC

EO® ESSENTIAL OILS

99.9% EFFECTIVE AGAINST MOST COMMON GERMS

EO® PRODUCTS, LLC. SAN RAFAEL, CA 94901
MADE IN THE USA FROM DOMESTIC AND GLOBALLY SOURCED COMPONENTS
800-570-3775 eoproducts.com
CERTIFIED ORGANIC BY CCOF

Inviting self-care

the scent benefit
French lavender draws you into the present moment, the now–an inspired daily dose of serenity.

the body benefit
Our non-drying hand spray, made with sugarcane-derived ethanol, cleanses and refreshes. 99.9% effective against most common germs.
Non-drying vegetable glycerin smooths skin without leaving a heavy residue behind.

We’ve consciously crafted accessible, timeless self-care rituals since 1995– all made with love, and without parabens, phthalates or synthetic fragrances.

Cruelty Free

CERTIFIED GLUTEN FREE